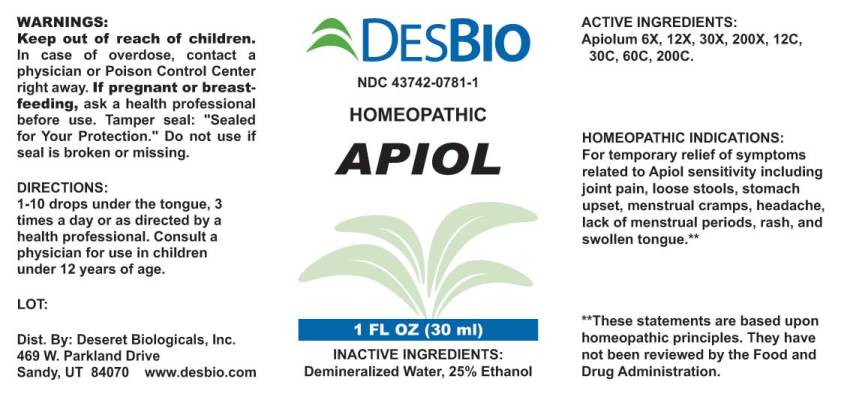 DRUG LABEL: Apiol
NDC: 43742-0781 | Form: LIQUID
Manufacturer: Deseret Biologicals, Inc.
Category: homeopathic | Type: HUMAN OTC DRUG LABEL
Date: 20250527

ACTIVE INGREDIENTS: APIOLE (PARSLEY) 6 [hp_X]/1 mL
INACTIVE INGREDIENTS: WATER; ALCOHOL

Drug Facts:

ACTIVE INGREDIENTS:

Apiolum 6X, 12X, 30X, 200X, 12C, 30C, 60C, 200C.

HOMEOPATHIC INDICATIONS:

For temporary relief of symptoms related to Apiol sensitivity including joint pain, loose stools, stomach upset, menstrual cramps, headache, lack of menstrual periods, rash, and swollen tongue. **

**These statements are based upon traditional homeopathic principles. They have not been reviewed by the Food and Drug Administration.

WARNINGS:

Keep out of reach of children. In case of overdose, contact a physician or Poison Control Center right away.

If pregnant or breast-feeding, seek advice of a health professional before use.

Tamper seal: "Sealed for Your Protection." Do not use if seal is broken or missing.

Keep out of reach of children. In case of overdose, contact physician or Poison Control Center right away.

DIRECTIONS:

1-10 drops under the tongue, 3 times a day or as directed by a health professional. Consult a physician for use in children under 12 years of age.

HOMEOPATHIC INDICATIONS:

For temporary relief of symptoms related to Apiol sensitivity including joint pain, loose stools, stomach upset, menstrual cramps, headache, lack of menstrual periods, rash, and swollen tongue. **

**These statements are based upon traditional homeopathic principles. They have not been reviewed by the Food and Drug Administration.

INACTIVE INGREDIENTS:

Demineralized Water, 25% Ethanol

QUESTIONS:

Dist. By: Deseret Biologicals, Inc.

469 W. Parkland Drive

Sandy, UT 84070 www.desbio.com

PACKAGE LABEL DISPLAY:

DESBIO

NDC 43742-0781-1

HOMEOPATHIC

APIOL

1 FL OZ (30 ml)